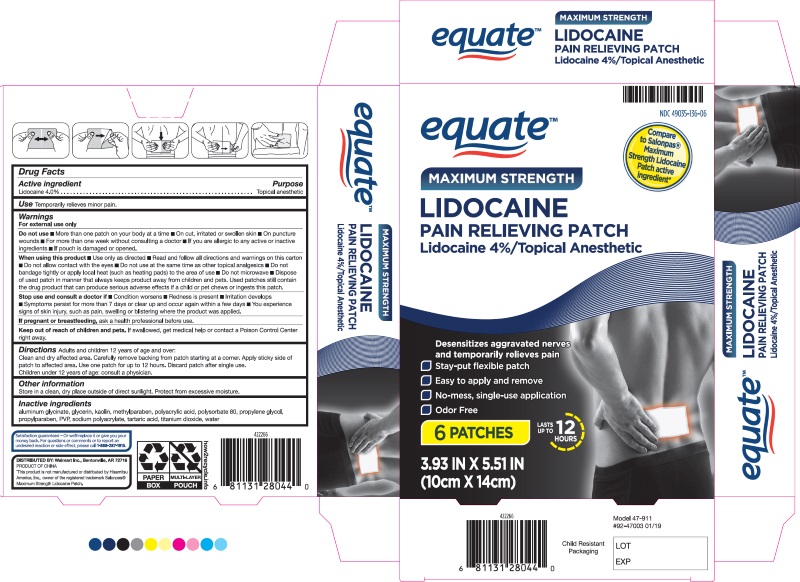 DRUG LABEL: PAIN RELIEF PATCHES
NDC: 49035-136 | Form: PATCH
Manufacturer: WALMART STORES INC
Category: otc | Type: HUMAN OTC DRUG LABEL
Date: 20260129

ACTIVE INGREDIENTS: LIDOCAINE 4 g/100 g
INACTIVE INGREDIENTS: ALUMINUM; GLYCERIN; KAOLIN; METHYLPARABEN; POLYACRYLIC ACID (300000 MW); POLYSORBATE 80; PROPYLENE GLYCOL; PROPYLPARABEN; POVIDONE, UNSPECIFIED; SODIUM POLYACRYLATE (2500000 MW); TARTARIC ACID; TITANIUM DIOXIDE; WATER

PAIN RELIEF PATCHES

Active Ingredients

Lidocaine 4% . . . . . . . . . . . . . . . . . . . . . . . . . . . . . . Topical Anesthetic

Purpose

Temporarily relieves minor pain.

Dosage and Administration

Directions Adults and children over 12 years:

■ clean and dry affected area

■ remove backing from patch by firmly grasping both ends and gently pulling until backing separates in middle

■ carefully remove smaller portion of backing from patch starting at corner

■ apply sticky side of patch to affected area

■ use one patch for up to 12 hours. Children under 12 years of age: consult a physician.

Warnings

For external use only.

Idications and Usage

Uses: Temporaily relieves minor pains.

When using this product

■ use only as directed

■ read and follow all directions and warnings on this carton

■ do not allow contact with the eyes

■ do not use at the same time as other topical analgesics

■ do not bandage tightly or apply local heat (such as heating pads) to the area of use

■ do not microwave

■ dispose of used patch in manner that always keeps product away from children and pets. Used patches still contain the drug product that can produce serious adverse effects if a child or pet chews or ingests this patch.

Stop use and consult a doctor

■ condition worsens

■ redness is present

■ irritation develops

■ symptoms persist for more than 7 days or clear up and occur again within a few days

■ you experience signs of skin injury, such as pain, swelling or blistering where the product was applied.

PREGNANCY OR BREAST FEEDING

If pregnant or breastfeeding, ask a health professional before use.

Do not Use

■ more than one patch on your body at a time

■ on cut, irritated or swollen skin

■ on puncture wounds

■ for more than one week without consulting a doctor

■ if you are allergic to any active or inactive ingredients

■ if pouch is damaged or opened.

Keep out of reach of children and pets.

If swallowed, get medical help or contact a Poison Control Center right away.

Other Safety Information

Store in a clean, dry place outside of direct sunlight. Protect from excessive moisture.

Inactive Ingredients

Aluminum Glycinate, Glycerin, Kaolin, Methylparaben, Polyacrylic Acid, Polysorbate 80, Propylene Glycol,
Propylparaben, PVP, Sodium Polyacrylate, Tartaric Acid, Titanium Dioxide, Water

Questions

Distributed by Walmart Inc.

Bentonville, AR 72716

Made in China